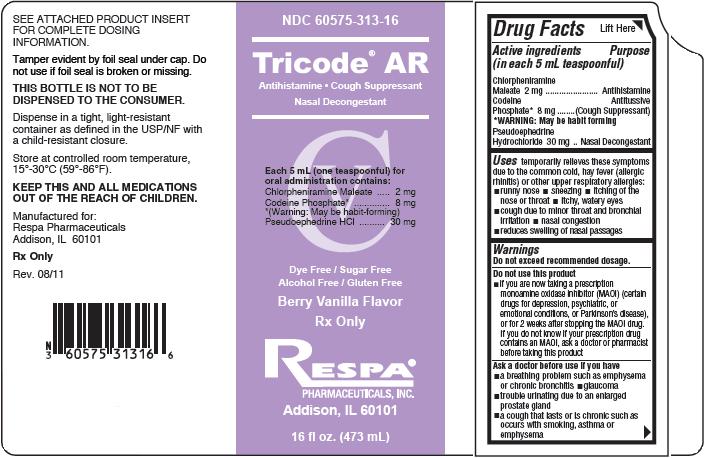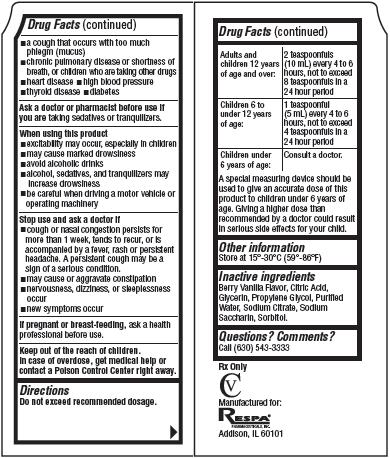 DRUG LABEL: Tricode
NDC: 60575-313 | Form: LIQUID
Manufacturer: Respa Pharmaceuticals, Inc.
Category: otc | Type: HUMAN OTC DRUG LABEL
Date: 20110909
DEA Schedule: CV

ACTIVE INGREDIENTS: Chlorpheniramine Maleate 2 mg/5 mL; Codeine Phosphate 8 mg/5 mL; Pseudoephedrine Hydrochloride 30 mg/5 mL
INACTIVE INGREDIENTS: Citric Acid; Glycerin; Propylene Glycol; Water; Sodium Citrate; Saccharin Sodium; Sorbitol

Tricode AR

Drug Facts

Active ingredients
(in each 5 mL teaspoonful)
Chlorpheniramine Maleate 2 mg
Codeine Phosphate* 8 mg
*WARNING: May be habit forming
Pseudoephedrine Hydrochloride 30 mg

Purpose

Antihistamine
Antitussive (Cough Suppressant)
Nasal Decongestant

Uses

temporarily relieves these symptoms due to the common cold, hay fever (allergic rhinitis) or other upper respiratory allergies:

- runny nose
- sneezing
- itching of the nose or throat
- itchy, watery eyes
- cough due to minor throat and bronchial irritation
- nasal congestion
- reduces swelling of nasal passages

Warnings

Do not exceed recommended dosage.

Do not use this product

- if you are now taking a prescription monoamine oxidase inhibitor (MAOI) (certain drugs for depression, psychiatric, or emotional conditions, or Parkinson's disease), or for 2 weeks after stopping the MAOI drug. If you do not know if your prescription drug contains an MAOI, ask a doctor or pharmacist before taking this product

Ask a doctor before use if you have

- a breathing problem such as emphysema or chronic bronchitis
- glaucoma
- trouble urinating due to an enlarged prostate gland
- a cough that lasts or is chronic such as occurs with smoking, asthma or emphysema
- a cough that occurs with too much phlegm (mucus)
- chronic pulmonary disease or shortness of breath, or children who are taking other drugs
- heart disease
- high blood pressure
- thyroid disease
- diabetes

Ask a doctor or pharmacist before use if you are

taking sedatives or tranquilizers.

When using this product

- excitability may occur, especially in children
- may cause marked drowsiness
- avoid alcoholic drinks
- alcohol, sedatives, and tranquilizers may increase drowsiness
- be careful when driving a motor vehicle or operating machinery

Stop use and ask a doctor if

- cough or nasal congestion persists for more than 1 week, tends to recur, or is accompanied by a fever, rash or persistent headache. A persistent cough may be a sign of a serious condition.
- may cause or aggravate constipation
- nervousness, dizziness, or sleeplessness occur
- new symptoms occur

If pregnant or breast-feeding,

ask a health professional before use.

Keep out of the reach of children.

In case of overdose, get medical help or contact a Poison Control Center right away.

Directions

Do not exceed recommended dosage.

Adults and children 12 years of age and over: | 2 teaspoonfuls (10 mL) every 4 to 6 hours, not to exceed 8 teaspoonfuls in a 24 hour period
Children 6 to under 12 years of age: | 1 teaspoonful (5 mL) every 4 to 6 hours, not to exceed 4 teaspoonfuls in a 24 hour period
Children under 6 years of age: | Consult a doctor.

A special measuring device should be used to give an accurate dose of this product to children under 6 years of age. Giving a higher dose than recommended by a doctor could result in serious side effects for your child.

Other information

Store at 15°- 30°C (59°- 86°F)

Inactive ingredients

Berry Vanilla Flavor, Citric Acid, Glycerin, Propylene Glycol, Purified Water, Sodium Citrate, Sodium Saccharin, Sorbitol.

Questions? Comments?

Call (630) 543-3333
Rx Only
CV
Manufactured for:
RESPA®
PHARMACEUTICALS, INC.
Addison, IL 60101

Product Packaging

The packaging below represents the labeling currently used:
Principal display panel and side panel for 473 mL label:
NDC 60575-313-16
____________________________________________
Tricode AR®
Antihistamine·Cough Suppressant
Nasal Decongestant
____________________________________________
Each 5 mL (one teaspoonful) for oral administration
contains:
Chlorpheniramine Maleate.................................2 mg
Codeine Phosphate*.........................................8 mg
*(Warning: May be habit-forming)
Pseudoephedrine HCl......................................30 mg
Dye Free / Sugar Free
Alcohol Free / Gluten Free
Berry Vanilla Flavor
Rx Only
RESPA®
PHARMACEUTICALS, INC.
Addison, IL 60101
16 fl oz. (473 mL)
SEE ATTACHED PRODUCT INSERT FOR COMPLETE
DOSING INFORMATION.
Tamper evident by foil seal under cap. Do not use if foil
seal is broken or missing.
THIS BOTTLE IS NOT TO BE DISPENSED TO THE CONSUMER.
Dispense in a tight, light-resistant container as defined in
the USP/NF with a child-resistant closure.
Store at controlled room temperature, 15°- 30°C (59°- 86°F).
KEEP THIS AND ALL MEDICATIONS OUT OF THE REACH
OF CHILDREN.
Manufactured for:
Respa Pharmaceuticals
Addision, IL 60101
Rx Only
Rev. 08/11